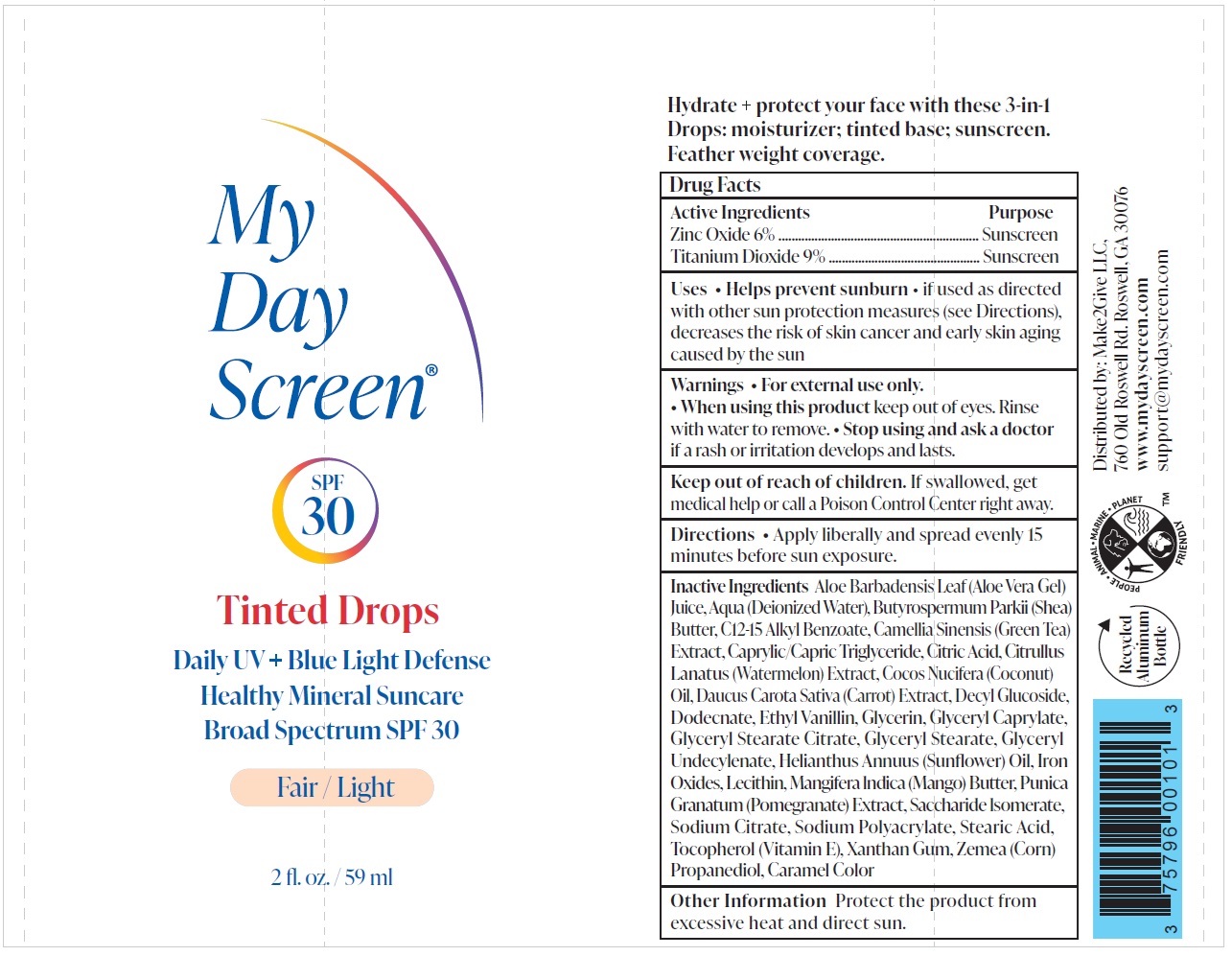 DRUG LABEL: Fair Light Tinted Drops
NDC: 75796-008 | Form: LOTION
Manufacturer: Make2Give LLC
Category: otc | Type: HUMAN OTC DRUG LABEL
Date: 20240806

ACTIVE INGREDIENTS: ZINC OXIDE 60 mg/1 mL; TITANIUM DIOXIDE 90 mg/1 mL
INACTIVE INGREDIENTS: ALOE VERA LEAF; WATER; SHEA BUTTER; ALKYL (C12-15) BENZOATE; GREEN TEA LEAF; MEDIUM-CHAIN TRIGLYCERIDES; CITRIC ACID MONOHYDRATE; WATERMELON; COCONUT; CARROT; DECYL GLUCOSIDE; ETHYL VANILLIN; GLYCERIN; GLYCERYL CAPRYLATE; GLYCERYL STEARATE CITRATE; GLYCERYL MONOSTEARATE; HELIANTHUS ANNUUS FLOWERING TOP; FERRIC OXIDE RED; MANGO; POMEGRANATE; SACCHARIDE ISOMERATE; SODIUM CITRATE; STEARIC ACID; .ALPHA.-TOCOPHEROL; XANTHAN GUM; CORN

Fair/Light Tinted Drops

Active Ingredients

Zinc Oxide 6%

Titanium Dioxide 9%

Purpose

Sunscreen

Uses

• Helps prevent sunburn• if used as directed with other sun protection measures (see Directions), decreases the risk of skin cancer and early skin aging caused by the sun

Warnings

• For external use only.

• When using this product

keep out of eyes. Rinse with water to remove.

• Stop using and ask a doctor

if a rash or irritation develops and lasts.

Keep out of reach of children.

If swallowed, get medical help or call a Poison Control Center right away.

Directions

• Apply liberally and spread evenly 15 minutes before sun exposure.

Inactive Ingredients

Aloe Barbadensis Leaf (Aloe Vera Gel) Juice, Aqua (Deionized Water), Butyroaperum Parkii (Shea) Butter, C12-15 Alkyl Benzoate, Camellia Sinensis (Green Tea) Extract, Caprylic/Capric Triglyceride, Citric Acid, Citrullus Lanatus (Watermelon) Extract, Cocos Nucifera (Coconut) Oil, Daucus Carota Sativa (Carrot¬) Extract, Decyl Glucoside, Dodecnate, Ethyl Vanilin, Glycerin, Glyceryl Caprylate, Glyceryl Stearate Citrate, Glyceryl Stearate, Glyceryl Undecylenate, Helianthus Annuus (Sunflower) Oil, Iron Oxides, Lecithin, Magnifera Indica (Mango) Butter, Punica Granatum (Pomegranate) Extract, Saccharide Isomerate Sodium Citrate, Sodium Polyacrylate, Stearic Acid, Tocopherol (Vitamin E), Xanthan Gum, Zemea (Corn) Propanediol, Caramel Color

Other Information

Protect the product from excessive heat and direct sun.